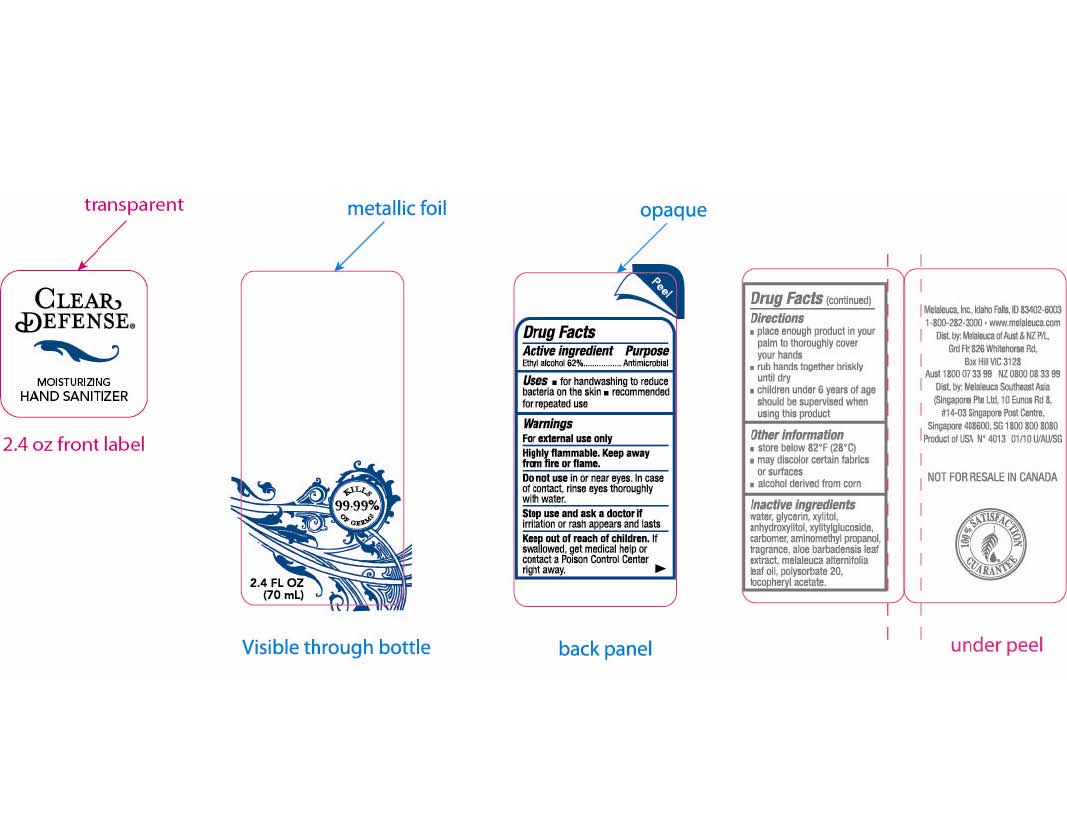 DRUG LABEL: Clear Defense
NDC: 54473-141 | Form: GEL
Manufacturer: Melaleuca, Inc.
Category: otc | Type: HUMAN OTC DRUG LABEL
Date: 20110117

ACTIVE INGREDIENTS: ALCOHOL 39.184 g/70 mL
INACTIVE INGREDIENTS: Water; Glycerin; XYLITOL; CARBOMER HOMOPOLYMER TYPE C; AMINOMETHYLPROPANOL; ALOE VERA LEAF; Tea Tree Oil; Polysorbate 20; ALPHA-TOCOPHEROL ACETATE

Clear Defense 2.4 oz Content of Label

Active Ingredient
Ethyl alcohol 62%

Purpose
Antimicrobial

Uses

- for handwashing to reduce bacteria on the skin
- recommended for repeated use

Warnings
For external use only
Highly flammable. Keep away from fire or flame.

Do not use in or near eyes. In case of contact, rinse eyes thoroughly with water.

Stop use and ask a doctor if irritation or rash appears and lasts

Keep out of reach of children. If swallowed, get medical help or contact a Poison Control Center right away.

Directions

- place enough product in your palm to thoroughly cover your hands
- rub hands together briskly until dry
- children under 6 years of age should be supervised when using this product

Other information

- Store below 82°F (28°C)

Other information

- may discolor certain fabrics or surfaces

Inactive ingredients
water, glycerin, xylitol, anhydroxylitol, xylitylglucoside, carbomer, aminomethyl propanol, fragrance, aloe barbadensis leaf extract, melaleuca alternifolia leaf oil, polysorbate 20, tocopheryl acetate